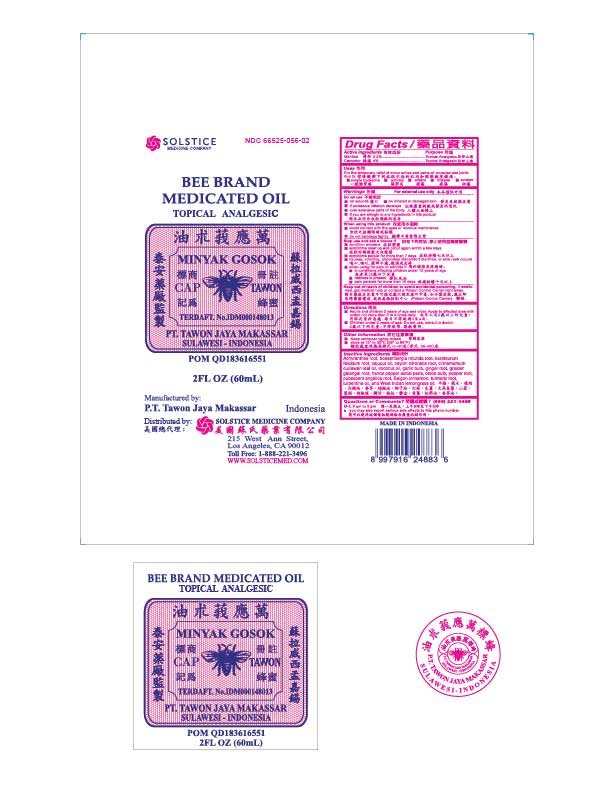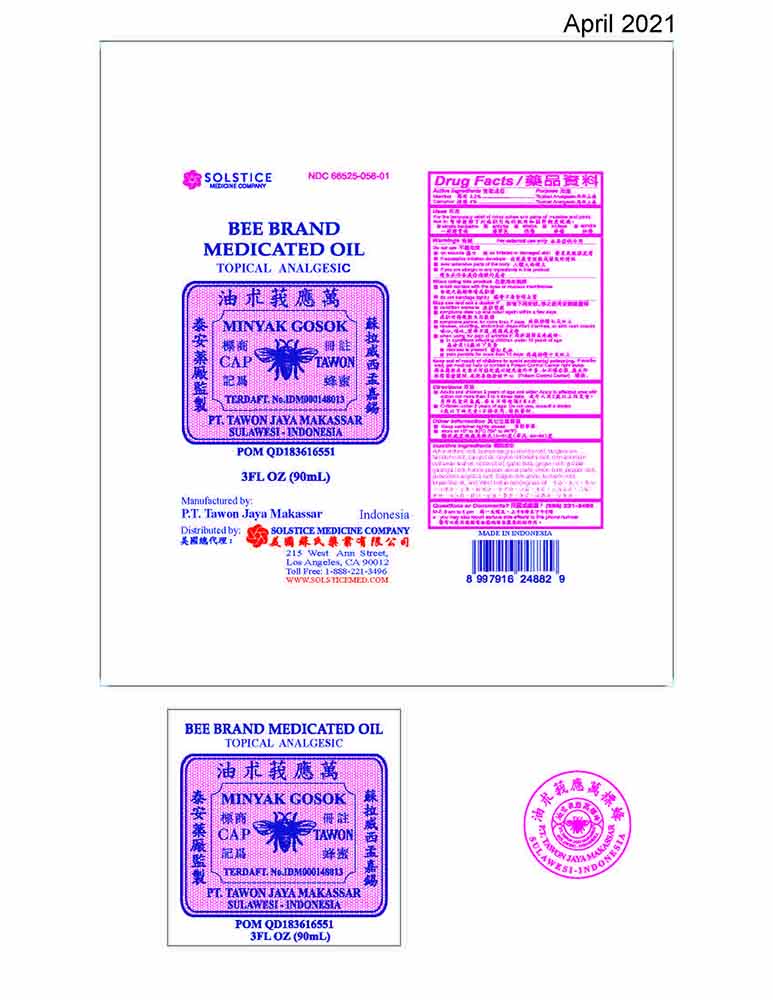 DRUG LABEL: BEE BRAND MEDICATED
NDC: 66525-056 | Form: OIL
Manufacturer: PT. TAWON JAYA MAKASSAR
Category: otc | Type: HUMAN OTC DRUG LABEL
Date: 20210630

ACTIVE INGREDIENTS: MENTHOL 2.2 mg/100 mL; CAMPHOR (SYNTHETIC) 4 mg/100 mL
INACTIVE INGREDIENTS: ACHYRANTHES BIDENTATA ROOT; BOESENBERGIA ROTUNDA ROOT; BUPLEURUM FALCATUM ROOT; CAJUPUT OIL; CYMBOPOGON NARDUS WHOLE; CINNAMOMUM CULILABAN LEAF OIL; COCONUT OIL; GARLIC; GINGER; GREATER GALANGAL; PIPER HANCEI TOP; ONION; PIPER NIGRUM WHOLE; ANGELICA PUBESCENS ROOT; CINNAMOMUM LOUREIROI WHOLE; TURMERIC; TURPENTINE OIL; CITRONELLA OIL

Drug Facts

Active ingredients
Menthol 2.2%
Camphor 4%

Purpose
External analgesic
External analgesic

Uses
For the temporary relief of minor aches and pains of muscles and joints due to:
■ simple backache
■ arthritis
■ strains
■ bruises
■ sprains

Warnings
For external use only

Do not use
■ on wounds
■ on irritated or damaged skin
■ if excessive irritation develops
■ over extensive parts of the body
■ if you are allergic to any ingredients in this product

When using this product
■ avoid contact with the eyes or mucous membranes
■ do not bandage tightly

Stop use and ask a doctor if
■ condition worsens
■ symptoms clear up and occur again within a few days
■ symptoms persist for more than 7 days
■ nausea, vomiting, abdominal discomfort, diarrhea, or skin rash occurs
■ when using for pain of arthritis if:
■ in conditions affecting children under 12 years of age
■ redness is present
■ pain persists for more than 10 days

Keep out of reach of children to avoid accidental poisoning. If swallowed, get medical help or contact a Poison Control Center right away.

Directions
■ Adults and children 2 years of age and older: Apply to affected area with cotton not more than 3 to 4 times daily.
■ Children under 2 years of age: Do not use, consult a doctor.

Other information
■ keep container tightly closed
■ store protected from light at 15 to 30 C (59 to 86 F)

Inactive ingredients
Achyranthes root, boesenbergia rotunda root, burpleurum falcatum root, cajuput oil, ceylon citronella root, cinnamomum culilawan leaf oil, coconut oil, garlic bulb, ginger root, greater galangal root, hance pepper aerial parts, onion bulb, pepper root, pubescent angelica root, Saigon cinnamon, turmeric root, turpentine oil, and West Indian lemongrass oil.

Questions or comments? (888) 221-3496 M-F 9 am to 5 pm
■ you may also report serious side effects to this phone number

PACKAGE LABEL

BEE BRAND MEDICATED OIL

NDC 66525-056-01

EXTERNAL ANALGESIC

3 FL OZ (90 mL)

PACKAGE LABEL

BEE BRAND MEDICATED OIL

NDC 66525-056-02

EXTERNAL ANALGESIC

2 FL OZ (60 mL)